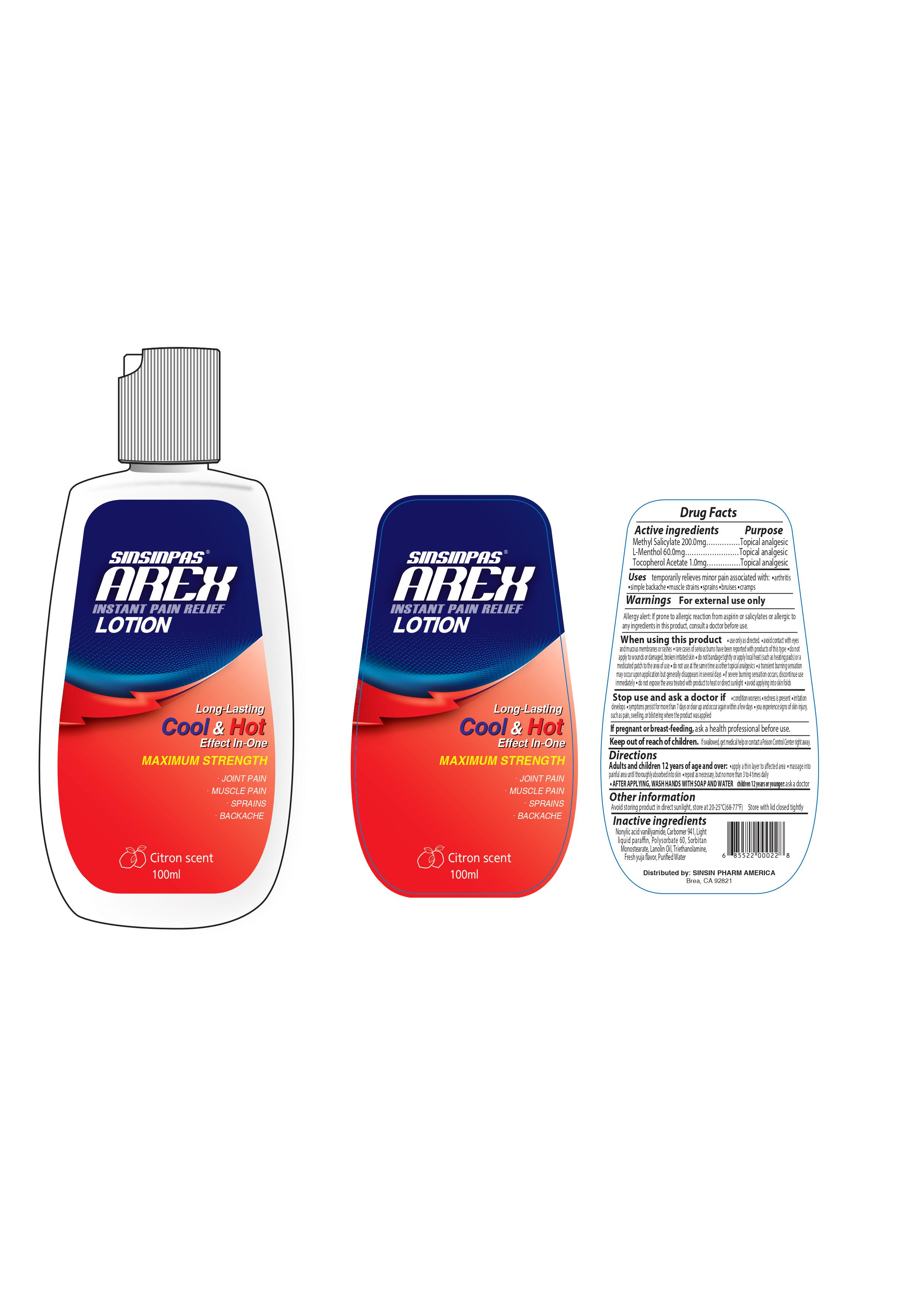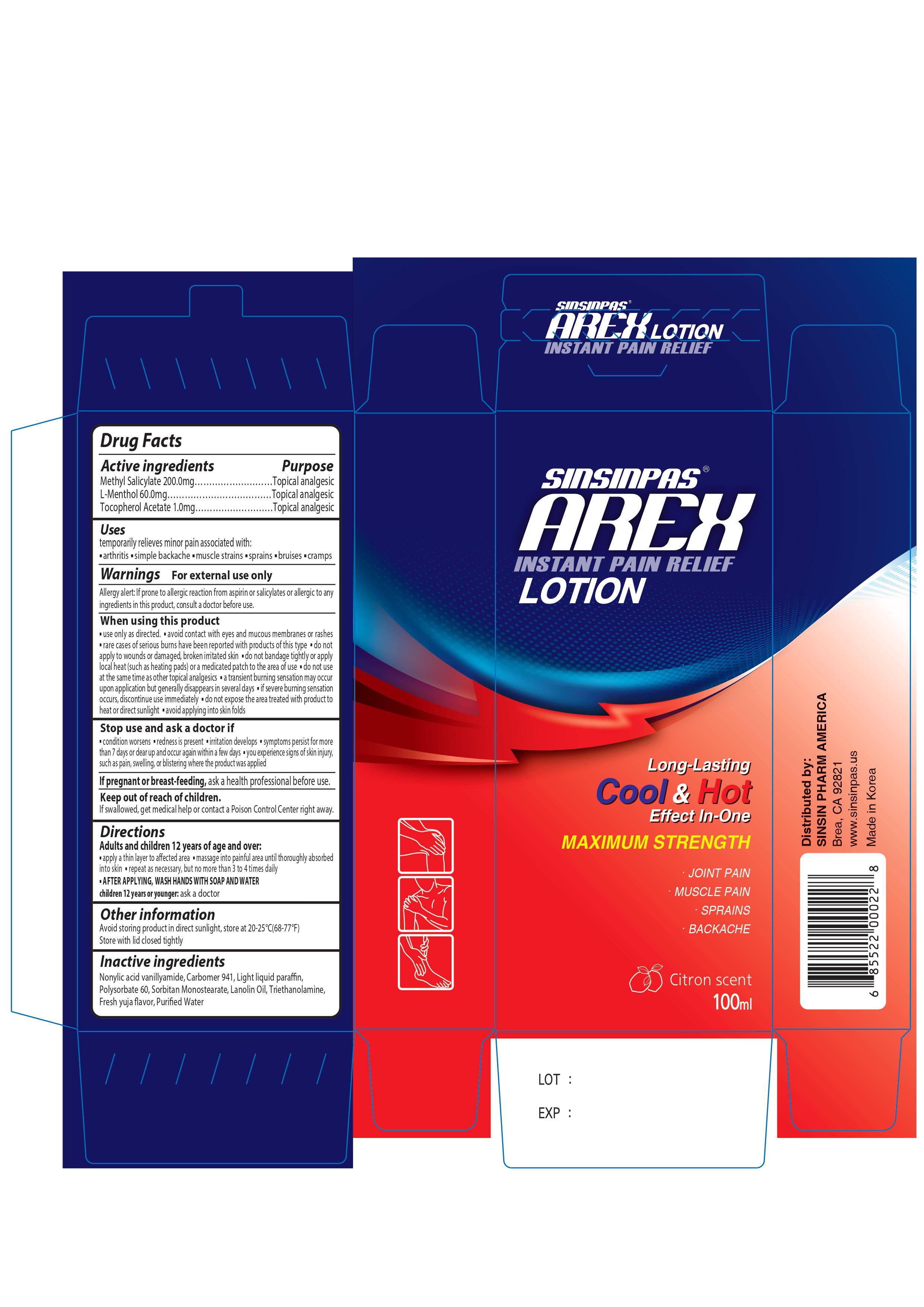 DRUG LABEL: SINSINPAS AREXLOTION
NDC: 55264-112 | Form: LOTION
Manufacturer: Sinsin Pharmaceutical Co., Ltd.
Category: otc | Type: HUMAN OTC DRUG LABEL
Date: 20240105

ACTIVE INGREDIENTS: METHYL SALICYLATE 200 mg/1 1; ALPHA-TOCOPHEROL ACETATE 1 mg/1 1; LEVOMENTHOL 60 mg/1 1
INACTIVE INGREDIENTS: POLYSORBATE 60; LANOLIN OIL; SORBITAN MONOSTEARATE; TROLAMINE; CITRUS JUNOS FRUIT; CARBOMER HOMOPOLYMER TYPE A (ALLYL PENTAERYTHRITOL CROSSLINKED); LIGHT MINERAL OIL; NONIVAMIDE; WATER

SINSINPAS AREX LOTION

Active Ingredients

Methyl Salicylate 200.0mg

L-Menthol 60.0mg

Tocopherol Acetate 1.0mg

Purpose

Topical Analgesic

Uses

Temporarily relieves minor pain associated with:

- Arthritis
- Simple backache
- Muscle strains
- Sprains
- Bruises
- Cramps

Warnings

For external use only

allergy alert: If prone to allergic reaction from aspirin or salicylates or allergic to any ingredients in this product, consult a doctor before use.

When using this product

- use only as directed
- avoid contact with eyes and mucous membranes or rashes
- rare cases of serious burns have been reported with products of this type
- do not apply to wounds or damaged, broken irritated skin
- do not bandage tightly or apply local heat (such as heating pads) or a medicated patch to the area of use
- do not use at the same time as other topical analgesics
- a transient burning sensation may occur upon application but generally disappears in several days
- if severe burning sensation occurs, discontinue use immediately
- do not expose the area treated with product to heat or direct sunlight
- avoid applying into skin folds

stop use and ask a doctor if

- condition worsens
- redness is present
- irritation develops
- symptoms persist for more than 7 days or clear up and occur again within a few days
- you experience signs of skin injury, such as pain, swelling, or blistering where the product was applied

If pregnant or breast-feeding, ask a health professional before use.

Keep out of reach of children.

If swallowed, get medical help or contact a Poison Control Center right away.

Keep out of reach of children

If swallowed, get medical help or contact a Poison Control Center (1-800-222-1222) right away.

Directions

Adults and children 12 years of age and over:

- apply a thin layer to affected area
- massage into painful area until thoroughly absorbed into skin

repeat as necessary, but no more than 3 to 4 times daily

- AFTER APPLYING, WASH HANDS WITH SOAP AND WATER

Children undress 12 years of age: ask a doctor

Other Information

- Avoid storing product in direct sunlight, store at 20-25C (68-77F)
- Store with lid closed tightly

Inactive Ingredients

Nonylic acid vanillyamide, Carbomer 941, Light liquid paraffin, Polysorbate 60, Sorbital Monostearate. Lanolin oil, Triethanolamine, Fresh yuja flavor, Purified water